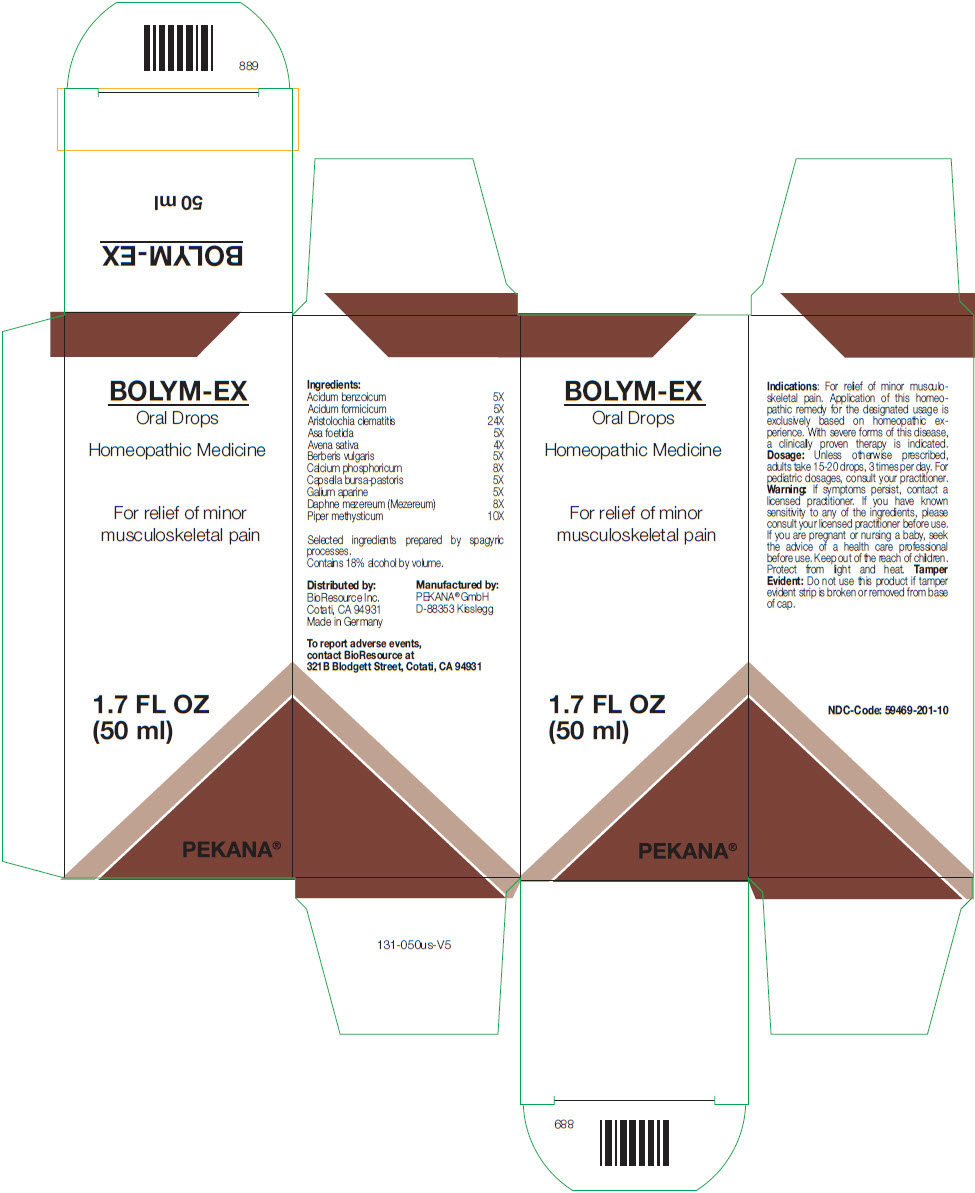 DRUG LABEL: BOLYM-EX Drops
NDC: 59469-201 | Form: LIQUID
Manufacturer: PEKANA Naturheilmittel GmbH
Category: homeopathic | Type: HUMAN OTC DRUG LABEL
Date: 20221223

ACTIVE INGREDIENTS: Benzoic Acid 5 [hp_X]/50 mL; Formic Acid 5 [hp_X]/50 mL; Aristolochia Clematitis Root 24 [hp_X]/50 mL; FERULA ASSA-FOETIDA RESIN 5 [hp_X]/50 mL; Avena Sativa Flowering Top 4 [hp_X]/50 mL; Berberis Vulgaris Root Bark 5 [hp_X]/50 mL; CALCIUM PHOSPHATE, UNSPECIFIED FORM 8 [hp_X]/50 mL; CAPSELLA BURSA-PASTORIS WHOLE 5 [hp_X]/50 mL; GALIUM APARINE WHOLE 5 [hp_X]/50 mL; Daphne Mezereum Bark 8 [hp_X]/50 mL; Macropiper Methysticum Root 10 [hp_X]/50 mL
INACTIVE INGREDIENTS: Alcohol

BOLYM-EX™ Oral Drops

Ingredients

Acidum benzoicum | 5X
Acidum formicicum | 5X
Aristolochia clematitis | 24X
Asa foetida | 5X
Avena sativa | 4X
Berberis vulgaris | 5X
Calcium phosphoricum | 8X
Capsella bursa-pastoris | 5X
Galium aparine | 5X
Daphne mezereum (Mezereum) | 8X
Piper methysticum | 10X

Selected ingredients prepared by spagyric processes.

INACTIVE INGREDIENT

Contains 18% alcohol by volume.

Indications

PURPOSE

For relief of minor musculoskeletal pain. Application of this homeopathic remedy for the designated usage is exclusively based on homeopathic experience. With severe forms of this disease, a clinically proven therapy is indicated.

Dosage

Unless otherwise prescribed, adults take 15-20 drops, 3 times per day. For pediatric dosages, consult your practitioner.

Warning

ASK DOCTOR

If symptoms persist, contact a licensed practitioner. If you have known sensitivity to any of the ingredients, please consult your licensed practitioner before use. If you are pregnant or nursing a baby, seek the advice of a health care professional before use.

Keep out of the reach of children.

STORAGE AND HANDLING

Protect from light and heat.

Tamper Evident

Do not use this product if tamper evident strip is broken or removed from base of cap.

Distributed by:
BioResource Inc.
Cotati, CA 94931

Manufactured by:
PEKANA® GmbH
D-88353 Kisslegg

PRINCIPAL DISPLAY PANEL - 50 ml Bottle Carton

BOLYM-EX
Oral Drops

Homeopathic Medicine

For relief of minor
musculoskeletal pain

1.7 FL OZ
(50 ml)

PEKANA®